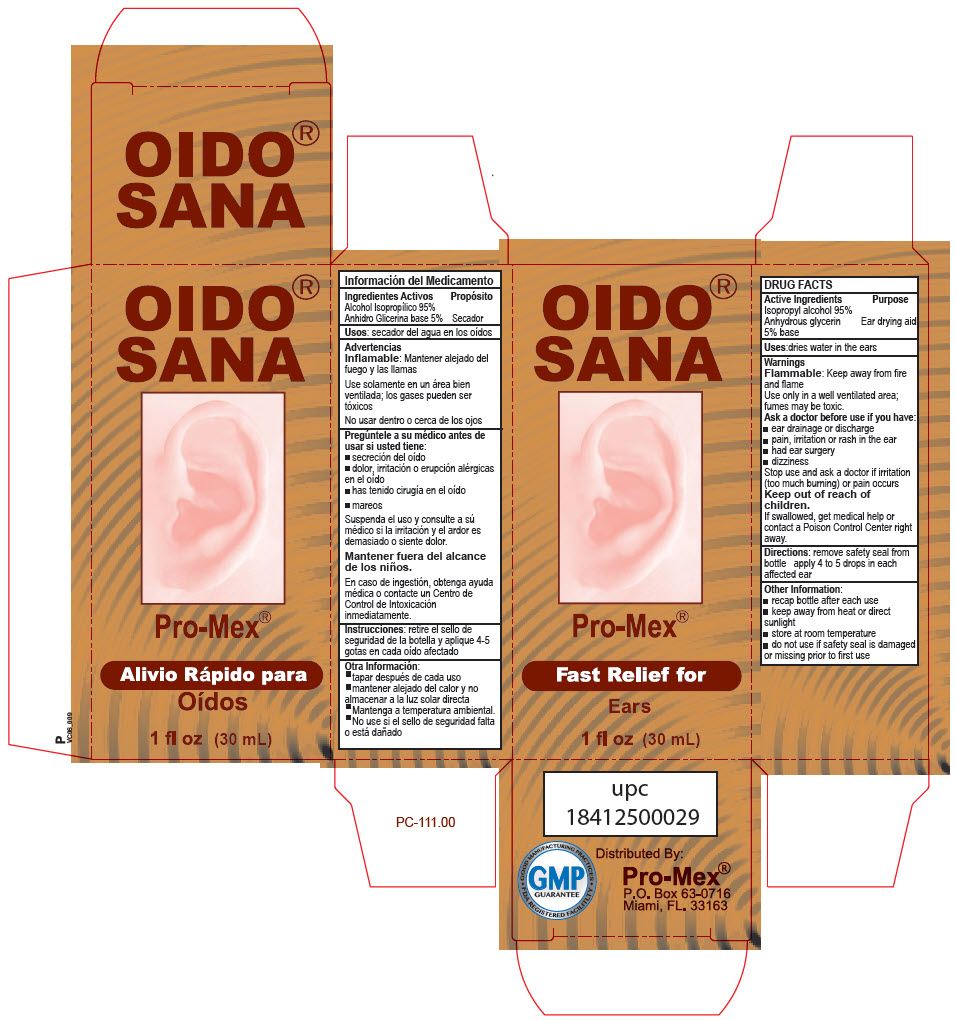 DRUG LABEL: OIDO SANA
NDC: 58988-1100 | Form: SOLUTION
Manufacturer: ProMex LLC
Category: otc | Type: HUMAN OTC DRUG LABEL
Date: 20241218

ACTIVE INGREDIENTS: ISOPROPYL ALCOHOL 0.95 g/1 mL
INACTIVE INGREDIENTS: GLYCERIN 0.05 g/1 mL

OIDO® SANA

DRUG FACTS

ACTIVE INGREDIENT

INACTIVE INGREDIENT

Active Ingredients: | Purpose
Isopropyl alcohol 95% | Ear drying aid
Anhydrous glycerin 5% base | Ear drying aid

Uses

dries water in the ears

Warnings

Flammable: Keep away from fire and flame

Use only in a well ventilated area; fumes may be toxic.

Ask a doctor before use if you have

- Ear drainage or discharge
- Pain, irritation or rash in the ear
- Had ear surgery
- Dizziness

Stop use and ask a doctor if irritation (too much burning) or pain occurs

Keep out of reach of children.

If swallowed, get medical help or contact a Poison Control Center right away.

Directions

remove safety seal from bottle, apply 4 to 5 drops in each affected ear.

Other information

- Recap bottle after each use
- Keep away from heat or direct sunlight
- Store at room temperature
- Do not use if safety seal is damaged or missing prior to first use

PRINCIPAL DISPLAY PANEL - 30 mL Bottle Carton

OIDO® SANA

Pro-Mex®

Fast Relief for

Ears

1 fl oz (30 mL)